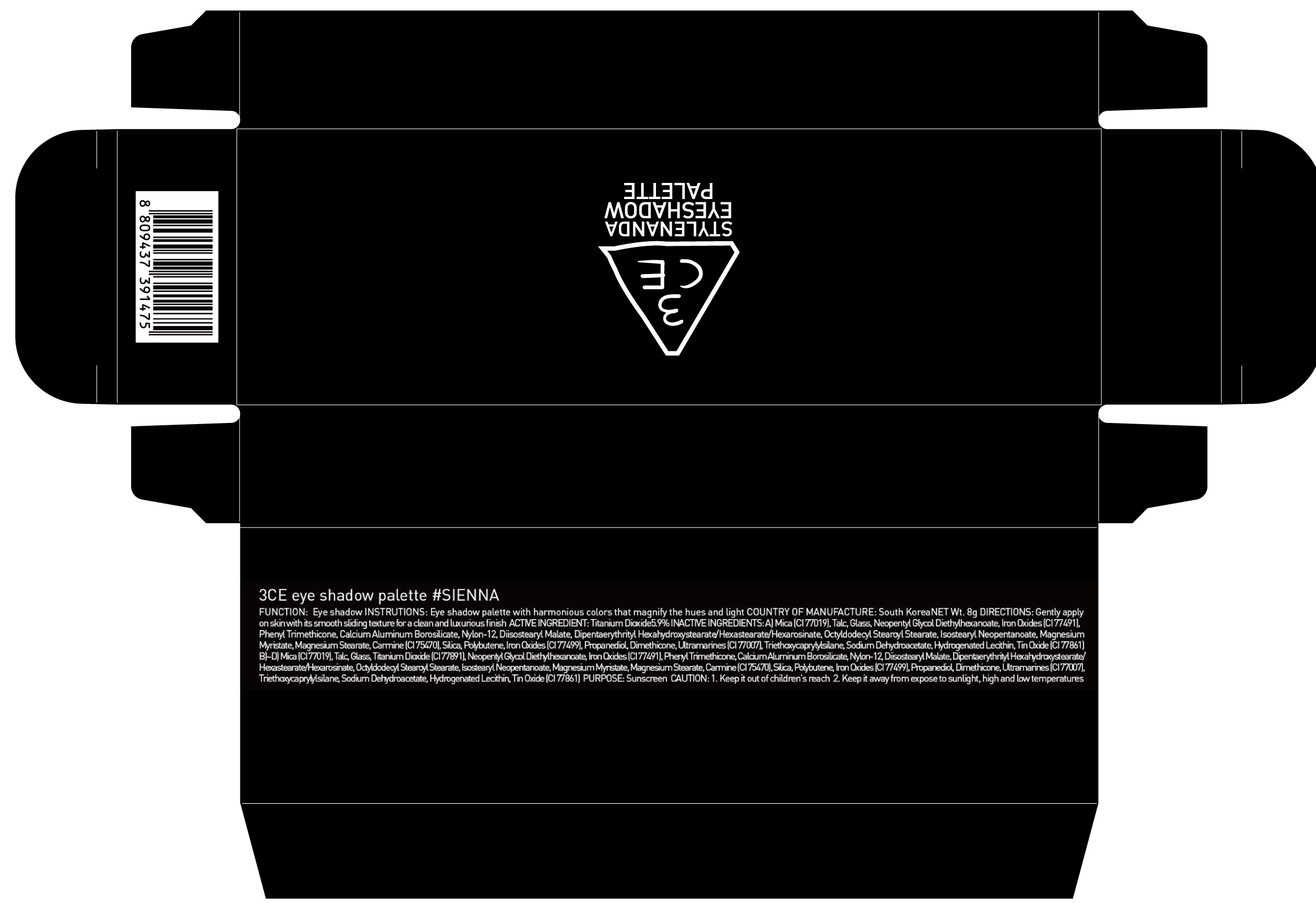 DRUG LABEL: 3CE EYE SHADOW PALETTE SIENNA
NDC: 60764-066 | Form: POWDER
Manufacturer: Nanda Co., Ltd
Category: otc | Type: HUMAN OTC DRUG LABEL
Date: 20161004

ACTIVE INGREDIENTS: Titanium Dioxide 0.47 g/8 g
INACTIVE INGREDIENTS: Mica; Talc

ACTIVE INGREDIENT

Active Ingredient: Titanium Dioxide 5.9%

INACTIVE INGREDIENT

Inactive Ingredients:

A) Mica (CI 77019), Talc, Glass, Neopentyl Glycol Diethylhexanoate, Iron Oxides (CI 77491), Phenyl Trimethicone, Calcium Aluminum Borosilicate, Nylon-12, Diisostearyl Malate, Dipentaerythrityl Hexahydroxystearate/Hexastearate/Hexarosinate, Octyldodecyl Stearoyl Stearate, Isostearyl Neopentanoate, Magnesium Myristate, Magnesium Stearate, Carmine (CI 75470), Silica, Polybutene, Iron Oxides (CI 77499), Propanediol, Dimethicone, Ultramarines (CI 77007), Triethoxycaprylylsilane, Sodium Dehydroacetate, Hydrogenated Lecithin, Tin Oxide (CI 77861)

B)~D) Mica (CI 77019), Talc, Glass, Titanium Dioxide (CI 77891), Neopentyl Glycol Diethylhexanoate, Iron Oxides (CI 77491), Phenyl Trimethicone, Calcium Aluminum Borosilicate, Nylon-12, Diisostearyl Malate, Dipentaerythrityl Hexahydroxystearate/Hexastearate/Hexarosinate, Octyldodecyl Stearoyl Stearate, Isostearyl Neopentanoate, Magnesium Myristate, Magnesium Stearate, Carmine (CI 75470), Silica, Polybutene, Iron Oxides (CI 77499), Propanediol, Dimethicone, Ultramarines (CI 77007), Triethoxycaprylylsilane, Sodium Dehydroacetate, Hydrogenated Lecithin, Tin Oxide (CI 77861)

PURPOSE

Purpose: Sunscreen

CAUTION

CAUTION: 1. Keep it out of children's reach 2. Keep it away from expose to sunlight, high and low temperatures.

DESCRIPTION

INSTRUCTIONS: Eye shadow palette with harmonious colors that magnify the hues and light.

Directions: Gently apply on skin with its smooth sliding texture for a clean and luxurious finish